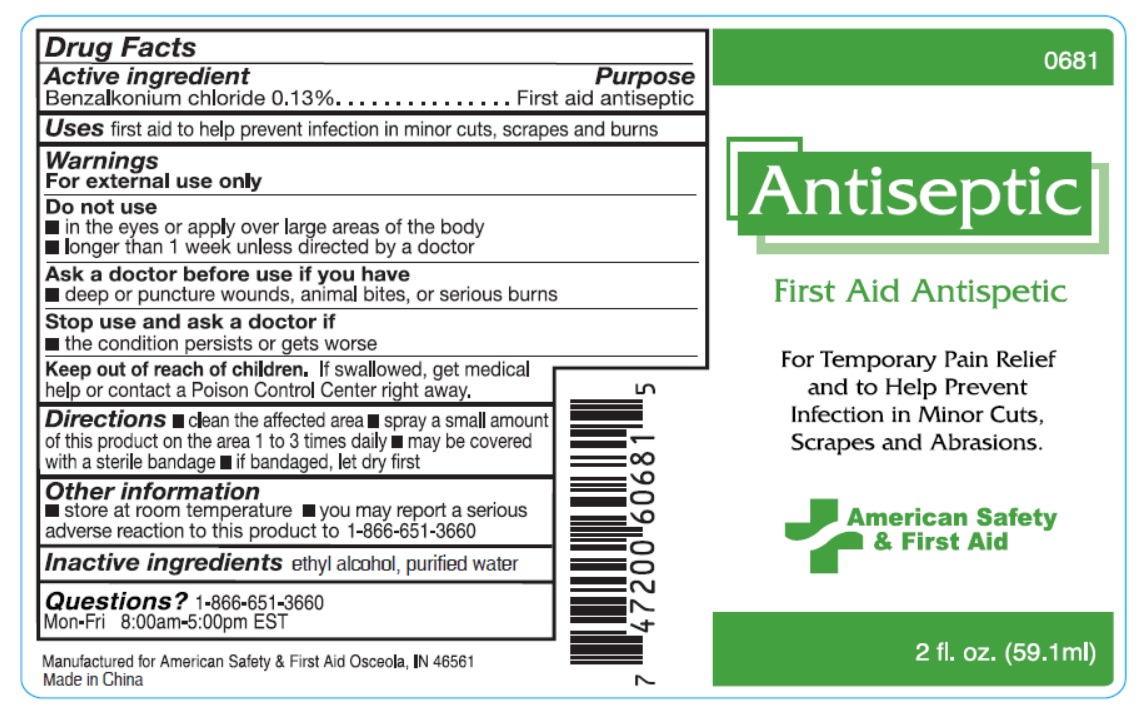 DRUG LABEL: First Aid Antispetic
NDC: 71927-011 | Form: SPRAY
Manufacturer: Orazen Inc
Category: otc | Type: HUMAN OTC DRUG LABEL
Date: 20240115

ACTIVE INGREDIENTS: BENZALKONIUM CHLORIDE 0.13 mg/1 mL
INACTIVE INGREDIENTS: WATER; ALCOHOL

First Aid Antispetic

Active ingredient

Benzalkonium chloride 0.13%

Purpose

First aid antiseptic

Uses

first aid to help prevent infection in minor cuts, scrapes and burns

Warnings

For external use only

Do not use

- in the eyes or apply over large areas of the body
- longer than 1 week unless directed by a doctor

Ask a doctor before use if you have

- deep or puncture wounds, animal bites, or serious burns

Stop use and ask a doctor if

- the condition persists or gets worse

Keep out of reach of children.

If swallowed, get medical help or contact a Poison Control Center right away.

Directions

- clean the affected area
- spray a small amount of this product on the area 1 to 3 times daily
- may be covered with a sterile bandage
- if bandaged, let dry first

Other information

- store at room temperature
- you may report a serious adverse reaction to this product to 1-866-651-3660

Inactive ingredients

ethyl alcohol, purified water

Questions?

1-866-651-3660
Mon-Fri 8:00am-5:00pm EST